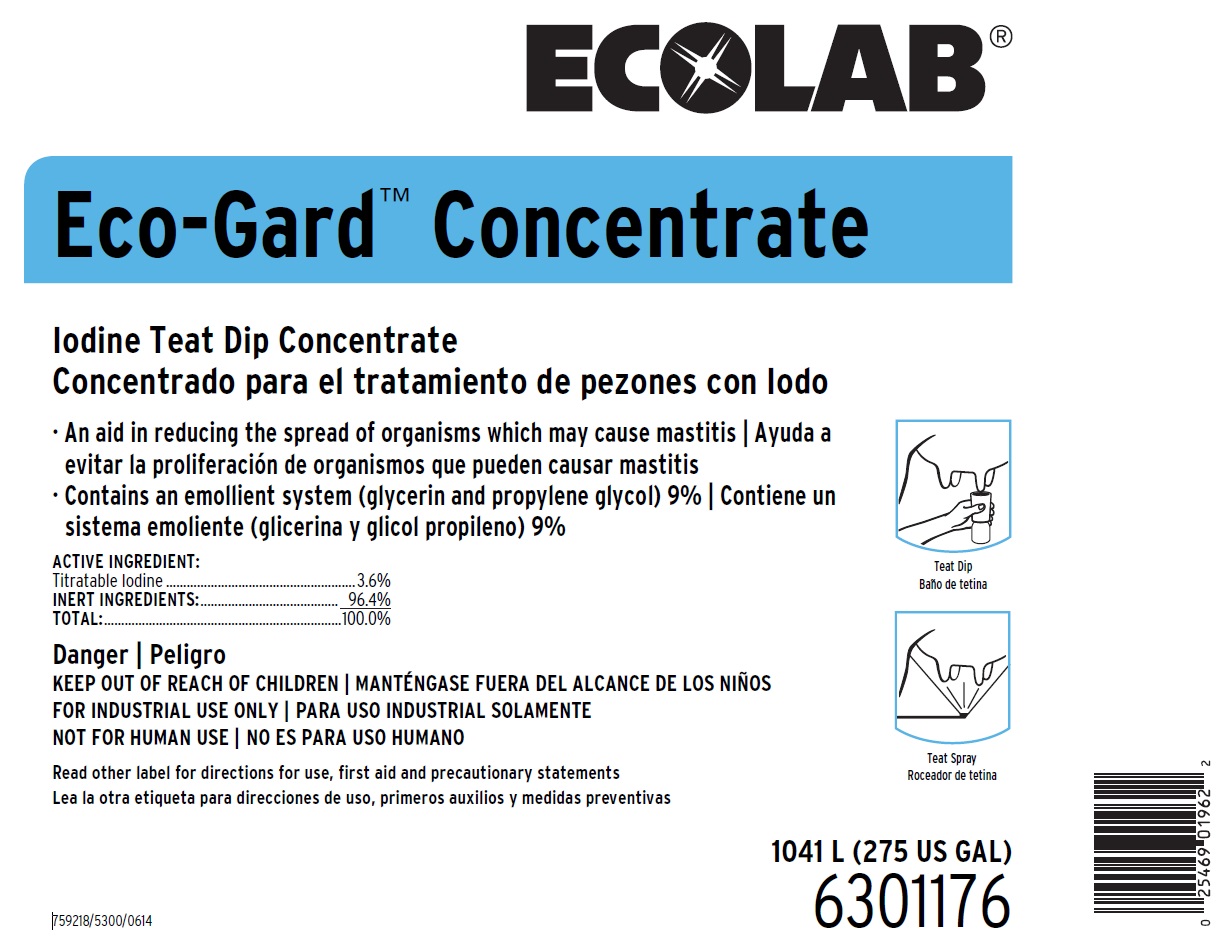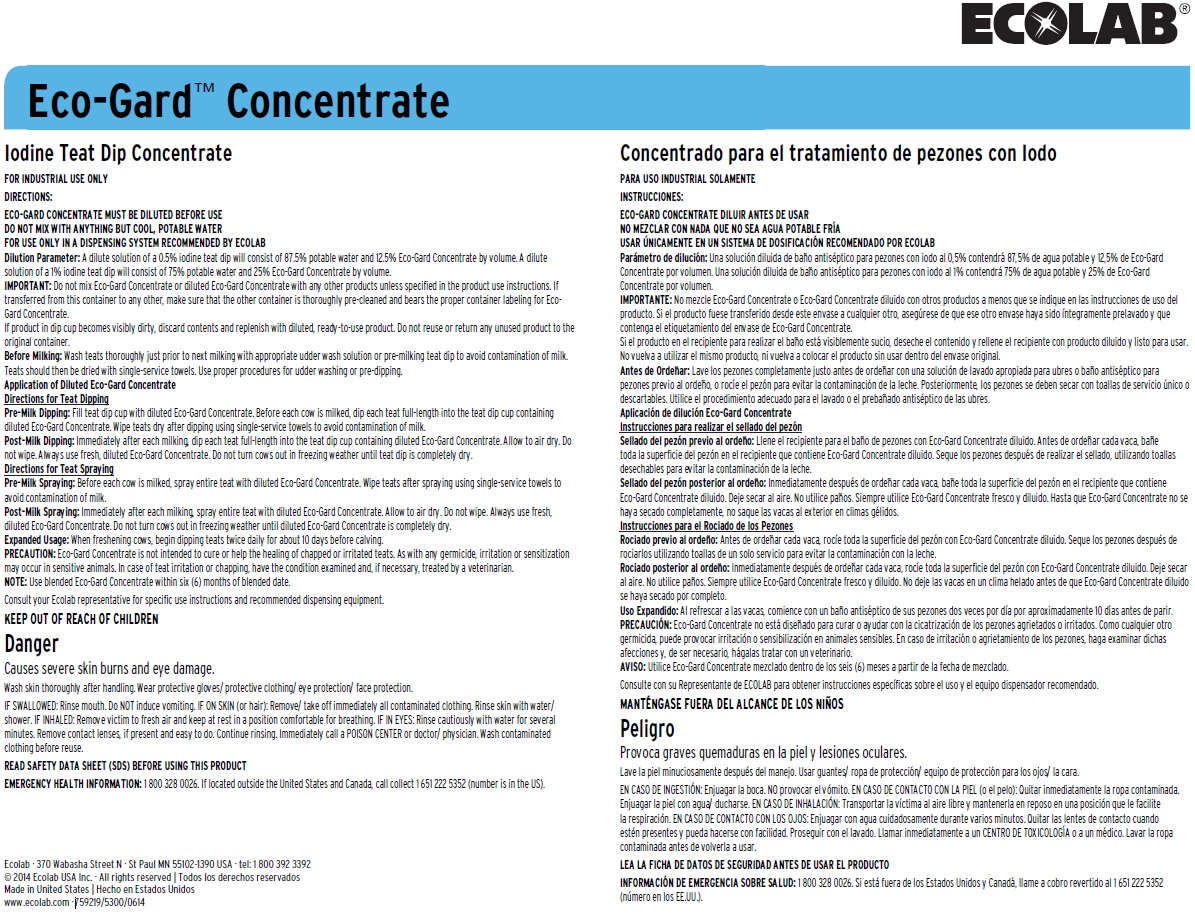 DRUG LABEL: ECO-GARD
NDC: 47593-402 | Form: SOLUTION
Manufacturer: Ecolab Inc.
Category: animal | Type: OTC ANIMAL DRUG LABEL
Date: 20250806

ACTIVE INGREDIENTS: IODINE 36 mg/1 mL
INACTIVE INGREDIENTS: WATER; PROPYLENE GLYCOL; GLYCERIN

SAFE HANDLING WARNING

Danger

KEEP OUT OF REACH OF CHILDREN

FOR INDUSTRIAL USE ONLY

NOT FOR HUMAN USE

Read other label for directions for use, first aid and precautionary statements

Causes severe skin burns and eye damage.

Wash skin thoroughly after handling. Wear protective gloves/ protective clothing/ eye protection/ face protection.

DIRECTIONS:
ECO-GARD CONCENTRATE MUST BE DILUTED BEFORE USE
DO NOT MIX WITH ANYTHING BUT COOL, POTABLE WATER
FOR USE ONLY IN A DISPENSING SYSTEM RECOMMENDED BY ECOLAB

Dilution Parameter: A dilute solution of a 0.5% iodine teat dip will consist of 87.5% potable water and 12.5% Eco-Gard Concentrate by volume. A dilute solution of a 1% iodine teat dip will consist of 75% potable water and 25% Eco-Gard Concentrate by volume.

IMPORTANT: Do not mix Eco-Gard Concentrate or diluted Eco-Gard Concentrate with any other products unless specified in the product use instructions. If transferred from this container to any other, make sure that the other container is thoroughly pre-cleaned and bears the proper container labeling for Eco- Gard Concentrate.

If product in dip cup becomes visibly dirty, discard contents and replenish with diluted, ready-to-use product. Do not reuse or return any unused product to the original container.

Before Milking: Wash teats thoroughly just prior to next milking with appropriate udder wash solution or pre-milking teat dip to avoid contamination of milk. Teats should then be dried with single-service towels. Use proper procedures for udder washing or pre-dipping.

Application of Diluted Eco-Gard Concentrate

Directions for Teat Dipping

Pre-Milk Dipping: Fill teat dip cup with diluted Eco-Gard Concentrate. Before each cow is milked, dip each teat full-length into the teat dip cup containing diluted Eco-Gard Concentrate. Wipe teats dry after dipping using single-service towels to avoid contamination of milk.

Post-Milk Dipping: Immediately after each milking, dip each teat full-length into the teat dip cup containing diluted Eco-Gard Concentrate. Allow to air dry. Do not wipe. Always use fresh, diluted Eco-Gard Concentrate. Do not turn cows out in freezing weather until teat dip is completely dry.
Directions for Teat Spraying

Pre-Milk Spraying: Before each cow is milked, spray entire teat with diluted Eco-Gard Concentrate. Wipe teats after spraying using single-service towels to avoid contamination of milk.

Post-Milk Spraying: Immediately after each milking, spray entire teat with diluted Eco-Gard Concentrate. Allow to air dry. Do not wipe. Always use fresh, diluted Eco-Gard Concentrate. Do not turn cows out in freezing weather until diluted Eco-Gard Concentrate is completely dry.

Expanded Usage: When freshening cows, begin dipping teats twice daily for about 10 days before calving.

PRECAUTION: Eco-Gard Concentrate is not intended to cure or help the healing of chapped or irritated teats. As with any germicide, irritation or sensitization may occur in sensitive animals. In case of teat irritation or chapping, have the condition examined and, if necessary, treated by a veterinarian.

NOTE: Use blended Eco-Gard Concentrate within six (6) months of blended date.

Consult your Ecolab representative for specific use instructions and recommended dispensing equipment.

OTHER SAFETY INFORMATION

IF SWALLOWED: Rinse mouth. Do NOT induce vomiting. IF ON SKIN (or hair): Remove/ take off immediately all contaminated clothing. Rinse skin with water/ shower. IF INHALED: Remove victim to fresh air and keep at rest in a position comfortable for breathing. IF IN EYES: Rinse cautiously with water for several minutes. Remove contact lenses, if present and easy to do. Continue rinsing. Immediately call a POISON CENTER or doctor/ physician. Wash contaminated clothing before reuse.

READ SAFETY DATA SHEET (SDS) BEFORE USING THIS PRODUCT

EMERGENCY HEALTH INFORMATION: 1 800 328 0026. If located outside the United States and Canada, call collect 1 651 222 5352 (number is in the US).

PRINCIPAL DISPLAY PANEL/REPRESENTATIVE LABEL

Eco-Gard™ Concentrate

Iodine Teat Dip Concentrate

An Aid in Reducing the Spread of Organisms which may cause mastitis

Contains an emollient system (glycerin and propylene glycol) 9%

ACTIVE INGREDIENT:

Titratable Iodine .............................................................3.6%

INERT INGREDIENTS ...................................................96.4%

TOTAL:.......................................................................100.0%

Danger

KEEP OUT OF REACH OF CHILDREN

FOR INDUSTRIAL USE ONLY

NOT FOR HUMAN USE

Read other label for directions for use, first aid and precautionary statements

1041 L (275 US GAL)

6301176

759218/5300/0614

Ecolab · 370 Wabasha Street N · St Paul MN 55102-1390 USA · tel: 1 800 392 3392

© 2014 Ecolab USA Inc. · All rights reserved

www.ecolab.com · 759219/5300/0614